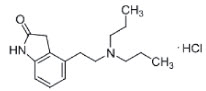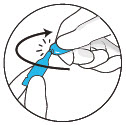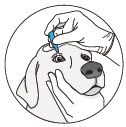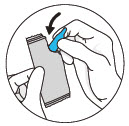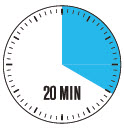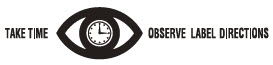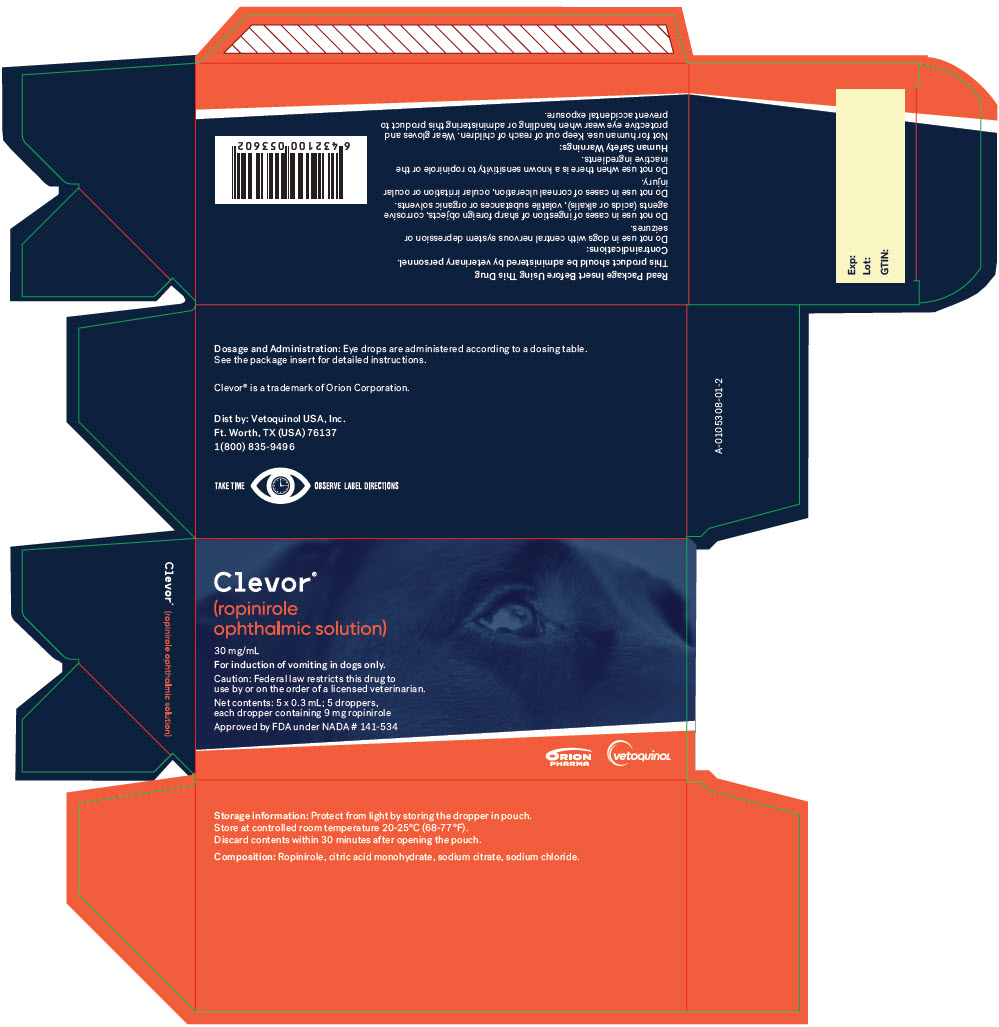 DRUG LABEL: CLEVOR
NDC: 17030-030 | Form: SOLUTION
Manufacturer: Vetoquinol USA, Inc.
Category: animal | Type: PRESCRIPTION ANIMAL DRUG LABEL
Date: 20220825

ACTIVE INGREDIENTS: ROPINIROLE HYDROCHLORIDE 30 mg/1 mL
INACTIVE INGREDIENTS: CITRIC ACID MONOHYDRATE; TRISODIUM CITRATE DIHYDRATE; SODIUM CHLORIDE; HYDROCHLORIC ACID; SODIUM HYDROXIDE; WATER

CLEVOR®

(ropinirole ophthalmic solution)
30 mg/mL
For ophthalmic use in dogs only

Single use dropper

CAUTION:

Federal law restricts this drug to use by or on the order of a licensed veterinarian.

DESCRIPTION:

CLEVOR (ropinirole ophthalmic solution) is a full dopamine agonist with selectivity for the dopamine D2-like receptor family. Each mL of CLEVOR contains 30 mg ropinirole (equivalent to 34.2 mg ropinirole hydrochloride). The chemical name of ropinirole hydrochloride is 2H-Indol-2- one, 4-[2- (dipropylamino)ethyl]-1,3-dihydro-, monohydrochloride. It is pale cream to yellow powder having a molecular weight of 296.84. The molecular formula is C16 H24 N2O ∙HCL and the structural formula is:

Inactive ingredients: citric acid monohydrate, sodium citrate, sodium chloride.

INDICATION:

For induction of vomiting in dogs.

DOSAGE AND ADMINISTRATION:

This product should be administered by veterinary personnel.

Dosing Instructions:

Administer the appropriate number of eye drops topically according to Table 1. The number of eye drops administered corresponding to body weight results in a target dose of 3.75 mg/m^2 (dose band 2.7 - 5.4 mg/m^2). If the dog does not vomit within 20 minutes of the first dose, then a second dose may be administered.

Table 1. Dose Administration
Body weight in kilograms | Body weight in pounds | Total number of eye drops | Example administration
1.8 - 5 | 4 - 11.1 | 1 | 1 drop into either left or right eye
5.1 - 10 | 11.2 - 22.1 | 2 | 1 drop each eye
10.1 - 20 | 22.2 - 44.1 | 3 | 2 drops in one eye and 1 drop in the other eye
20.1 - 35 | 44.2 - 77.2 | 4 | 2 drops in each eye
35.1 - 60 | 77.3 - 132.3 | 6 | An initial dose of 2 drops in each eye, followed 2 minutes later by 1 drop in each eye
60.1 - 100 | 132.4 - 220.5 | 8 | An initial dose of 2 drops in each eye, followed 2 minutes later by 2 drops in each eye

Dose Administration:

- Wear gloves and protective eye wear when handling or administering this product to prevent accidental exposure.
- Open the dropper by twisting off the tail.

- Keep the dog's head steady in a slightly upright position.
- Hold the dropper in an upright position without touching the eye.
- Rest your finger on the forehead of your dog to maintain the distance between the dropper and the eye.
- Squeeze the prescribed number of drops in to the eye(s).

- CLEVOR is a single use dropper and is light sensitive.
- After administration, with gloves on, return the dropper to the aluminum pouch and place in the carton.

- If the dog does not vomit, a second dose can be given 20 minutes after administration of the first dose.
- This second dose is the same number of drops as the first dose.
- Thirty minutes after opening, with gloves on, dispose of dropper, aluminum pouch, and carton.

Refer to the Animal Safety Warnings section for treatment of protracted vomiting.

CONTRAINDICATIONS:

Do not use in dogs with central nervous system depression or seizures.

Do not use in cases of ingestion of sharp foreign objects, corrosive agents (acids or alkalis), volatile substances or organic solvents.

Do not use in cases with corneal ulceration, ocular irritation, or ocular injury.

Do not use when there is a known sensitivity to ropinirole or the inactive ingredients.

WARNINGS:

Human Safety Warnings:

Not for use in humans. Keep out of reach of children.

Wear gloves and protective eye wear when handling or administering this product to prevent accidental exposure. In case of accidental eye, oral or skin exposure, flush with water. If wearing contact lenses, eyes should be rinsed first, then remove contact lenses and continue rinsing. Remove contaminated clothing. Ropinirole is a dopamine agonist. Seek medical attention if accidental exposure occurs and show the package insert or label to the physician. Exposure to this drug may cause adverse reactions such as headache, nausea, vomiting, dizziness, orthostatic hypotension, and sleepiness. Avoid contact with the product if pregnant, planning to become pregnant, or breast-feeding, as exposure has been shown to have adverse effects on embryo-fetal development based on rodent studies.

Animal Safety Warnings:

This product should be administered by veterinary personnel.

Dogs should be monitored for CLEVOR-associated clinical signs, including protracted vomiting, salivation, muscle tremors, evidence of abdominal discomfort, lethargy, transient tachycardia, transient decrease in blood pressure and signs of ocular irritation, including conjunctival hyperemia, mild blepharospasm, and protrusion of the third eyelid. These clinical signs are related to the pharmacological action of ropinirole.

To stop protracted vomiting, administer metoclopramide (dopamine D2 antagonist) at a dose of 0.5 mg/kg intravenously (IV) or subcutaneously (SQ). Metoclopramide also decreases the prevalence of most CLEVOR-associated clinical signs.

PRECAUTIONS:

The safe use of CLEVOR has not been evaluated in dogs with cardiac disease or cardiovascular compromise. CLEVOR can cause transient tachycardia and transient decreased systolic blood pressure.

The safe use of CLEVOR has not been evaluated in dogs with hepatic impairment. CLEVOR is metabolized by the liver.

The safe use of CLEVOR has not been evaluated in dogs younger than 4.5 months of age and weight less than 4 pounds.

The safe use of CLEVOR has not been evaluated in dogs that are pregnant, lactating, or intended for breeding.

ADVERSE REACTIONS:

Safety was evaluated during a field study that enrolled 132 dogs (100 in the CLEVOR group and 32 in the vehicle control group). CLEVOR was administered as drops into the eyes at the dose as directed by the dosing table (see DOSAGE AND ADMINISTRATION). The following table shows the number of dogs exhibiting ocular, systemic, and clinical pathology adverse reactions.

Table 2: Adverse Reactions Reported During the Study (all dogs)
Organ System | Adverse Reaction | CLEVOR (N=100) | Vehicle control (N=32)
Ocular | Conjunctival hyperemia [Assessment performed 30 minutes after dose administration] | 51 (51%) | 6 (19%)
Ocular | Protrusion of the third eyelid | 38 (38%) | 1 (3%)
Ocular | Conjunctival discharge | 30 (30%) | 1 (3%)
Ocular | Blepharospasm | 19 (19%) | 0
Ocular | Conjunctival swelling | 3 (3%) | 0
Ocular | Scratching/rubbing of eyes | 4 (4%) | 0
Ocular | Corneal ulceration | 1 (1%) | 0
Ocular | Corneal fluorescein uptake without corneal ulceration | 1 (1%) | 0
Systemic | Lethargy | 41 (41%) | 0
Systemic | Tachycardia (>160 beats per minute), [Tachycardia resolved for most dogs within 4 hours after dose administration] | 14 (14%) | 0
Systemic | Vomiting duration longer than one hour | 8 (8%) | 0
Systemic | Salivation | 3 (3%) | 1 (3%)
Systemic | Trembling | 3 (3%) | 0
Systemic | Diarrhea or soft stool | 2 (2%) | 1 (3%)
Systemic | Anxious | 1 (1%) | 0
Systemic | Borborygmi | 1 (1%) | 0
Clinical Pathology | Crystalluria [Urinalysis results were reported for only 86 dogs (66 administered CLEVOR and 20 control)] | 13 (20%) | 3 (15%)
Clinical Pathology | Pyuriac | 12 (18%) | 3 (15%)
Clinical Pathology | Increased liver enzymes [All three dogs had elevated alanine aminotransferase. Additionally, one of the dogs also had an elevated aspartate aminotransferase and another of the dogs also had an elevated alkaline phosphatase and total bilirubin.] | 3 (3%) | 0
Clinical Pathology | Decreased blood glucose | 2 (2%) | 0
Clinical Pathology | Increased prothrombin time | 1 (1%) | 0

Note: If any animal experienced the event more than once, only the first occurrence was tabulated.

To report suspected adverse events call 1(800) 835-9496, for technical assistance or to obtain a copy of the SDS, contact Vetoquinol USA, Inc. at 1 (800) 267-5707 or www.vetoquinolusa.com.

For additional information about adverse drug experience reporting for animal drugs, contact FDA at 1-888-FDA-VETS or online at www.fda.gov/reportanimalae.

CLINICAL PHARMACOLOGY:

Ropinirole is a full dopamine agonist with selectivity for the dopamine D2-like receptor family. Ropinirole induces vomiting by activating the D2-like receptors in the chemoreceptor trigger zone, located in the area postrema, which transmits the information to the vomiting center to trigger vomiting.

Absorption: Ropinirole solution is rapidly absorbed after ocular administration in dogs. The systemic bioavailability of the drug by this route of administration is 18 to 28%. The maximum concentration (Cmax) after ocular administration at the target dose level of 3.75 mg/m^2 was 25.6 ± 7.75 ng/mL at 10 to 20 minutes (Tmax). Cmax in dogs that had to be re-dosed 20 minutes after the first administration was 34.2 ± 11.0 ng/mL at a Tmax of 10 to 60 minutes. Vomiting generally starts before the Cmax in plasma is reached. No direct correlation between the drug concentration in plasma and the duration of vomiting was observed after ocular administration.

Distribution: Ropinirole has a relatively large apparent volume of distribution. In dogs the volume of distribution (Vd) was 5.63 ± 1.40 L/kg after intravenous administration. The fraction bound to plasma proteins in dogs has been reported as 37%.^1

Metabolism and Elimination: Ropinirole is mainly eliminated by hepatic metabolism.^1,2

The half-life of elimination (t½) is approximately 4 hours after intravenous administration to dogs. Biotransformation occurs by dealkylation, hydroxylation and subsequent conjugation with glucuronic acid or oxidation to carboxylic acid.^3,4 Excretion occurs mainly as metabolites in the urine.

EFFECTIVENESS:

Effectiveness was demonstrated in a multi-center, vehicle-controlled, randomized and masked field study in client-owned dogs of various breeds. Dogs enrolled in the study were 7 months to 15 years of age and weighed 1.9 to 66.3 kg. In this study, 132 dogs were enrolled and randomized to treatment with CLEVOR (n=100) or vehicle control (n=32). The effectiveness evaluation population included 99 CLEVOR treated dogs and 29 vehicle control dogs.

Dogs received a dose administered as drops into the eye(s) approximately 1 hour after a meal. The dose was administered according to weight (see Dosage and Administration). If the dog did not vomit within 20 minutes of the first dose, a second dose was administered.

Treatment success was defined for each dog as vomiting within 30 minutes of treatment. The percent of treatment success for CLEVOR was greater than vehicle control. The confidence interval around the estimated success rate 0.969 was (0.831, 0.995).

Table 3. Number and % Effectiveness for CLEVOR and Vehicle Control
Time to Vomit | CLEVOR ® (n=99) | Vehicle Control (n=29)
0-30 minutes | 94 (95%) | 0 (0%)

The time to first vomition, the number of times the dog vomited, and the description of vomit were evaluated as secondary variables and support the effectiveness of CLEVOR for induction of vomiting in dogs. Eighty-five dogs (86%) in the CLEVOR group vomited within 20 minutes and therefore did not require a second dose. The time to first vomition ranged from 3 minutes to 37 minutes with a mean of 12 minutes. The duration between first and last vomiting episodes ranged from 0 to 108 minutes with a mean duration of 23 minutes. Eight dogs had vomiting episodes over a duration longer than an hour. Five of these eight dogs were administered an antiemetic (metoclopramide). The number of vomits ranged from 0 to 13 vomits with a mean of 4.8 vomits per dog. Of the dogs that vomited, 96% of the dogs produced a vomit containing the meal that had been fed approximately one hour prior to CLEVOR administration.

ANIMAL SAFETY:

In a laboratory study, 32 healthy Beagle dogs aged 4.5 - 5.5 months were administered CLEVOR at 1X, 3X, and 5X the proposed labeled dose of 2.7-5.4 mg/m^2 (0.23-0.31 mg/kg), repeated once after 20 minutes [total dose of 8.5-10.6 mg/m^2 (0.45-0.62 mg/kg)] (dose divided between both eyes), for 3 days.

Dogs in the CLEVOR groups generally vomited within 5 - 10 minutes of dose administration and none of the dogs in the saline group vomited. Vomiting occurred as often as every 1 - 2 minutes and lasted 1 - 2 hours. Additional systemic effects of CLEVOR included retching, salivation, hunched posture, tremors, labored breathing, lethargy, ventral and lateral recumbency, transient tachycardia, transient decrease in indirect systolic blood pressure (but not less than 125 mmHg), and a dose dependent decrease in body temperature (although all temperatures remained within normal limits). Local ocular effects of CLEVOR included ocular discharge, hyperemia, conjunctival erythema, blepharospasm, ptosis, third eyelid elevation, and positive corneal fluorescein staining. All CLEVOR-related observations resolved within 6 hours post-dosing. There was a dose dependent decrease in food consumption for dogs in the CLEVOR groups. Some dogs in the CLEVOR groups also had slight decreases in body weight. There were no effects on gross or microscopic pathology.

STORAGE CONDITIONS:

Store in the original package in order to protect from light at controlled room temperature 20-25˚C (68-77˚F) with excursions permitted to 15-30˚C (59-86˚F). After the first dosing, the opened dropper should be kept in the aluminum pouch. The content should be used and discarded within 30 minutes after opening the aluminum pouch.

HOW SUPPLIED:

CLEVOR is packaged in a unit-dose low density polyethylene dropper. Each dropper is packaged in an individual aluminum foil laminate pouch. The pouch/pouches are further packaged in a carton with the same number of leaflets as the number of unit-dose droppers.

Package sizes: Single package of 1 unit-dose dropper and multipackage of 5 unit-dose droppers.

REFERENCES:

1. Swagzdis J, et. al., (1986) Pharmacokinetics of dopamine-2 agonists in rats and dogs.
J Pharm Sci 75 (10): 925-928.

2. Ramji J et al., (1999) Disposition of ropinirole in animals and man. Xenobiotica. 29 (3): 311-325.

3. Mico B et al., (1986) Functional group metabolism of dopamine-2 agonists: Conversion of 4-(2-Di-n-propylaminoethyl)-2-(3H)-indolone to 4-(2-Di-n-propylaminoethyl)-7-hydroxy-2-(3H)-indolone. J Pharm Sci 75 (10): 929-933.

4. Reavill C et al., (2000) Comparative pharmacological study of ropinirole (SKF-101468) and its metabolites in rats.
J Pharm Pharmacol 52 (9): 1129-1135.

CLEVOR is a trademark of Orion Corporation

Manufactured by:
Orion Corporation

Distributed by:
Vetoquinol USA, Inc.
Ft. Worth, TX (USA) 76137
1 (800) 267-5707
www.vetoquinolusa.com

Issued 06/2020

Approved by FDA under NADA # 141-534

A-0105307-01-1

PRINCIPAL DISPLAY PANEL - 5 x 0.3 mL Bottle Box

Clevor®
(ropinirole
ophthalmic solution)

30 mg/mL

For induction of vomiting in dogs only.

Caution: Federal law restricts this drug to
use by or on the order of a licensed veterinarian.

Net contents: 5 x 0.3 mL; 5 droppers,
each dropper containing 9 mg ropinirole

Approved by FDA under NADA # 141-534

ORION
PHARMA

vetoquinol